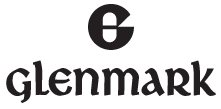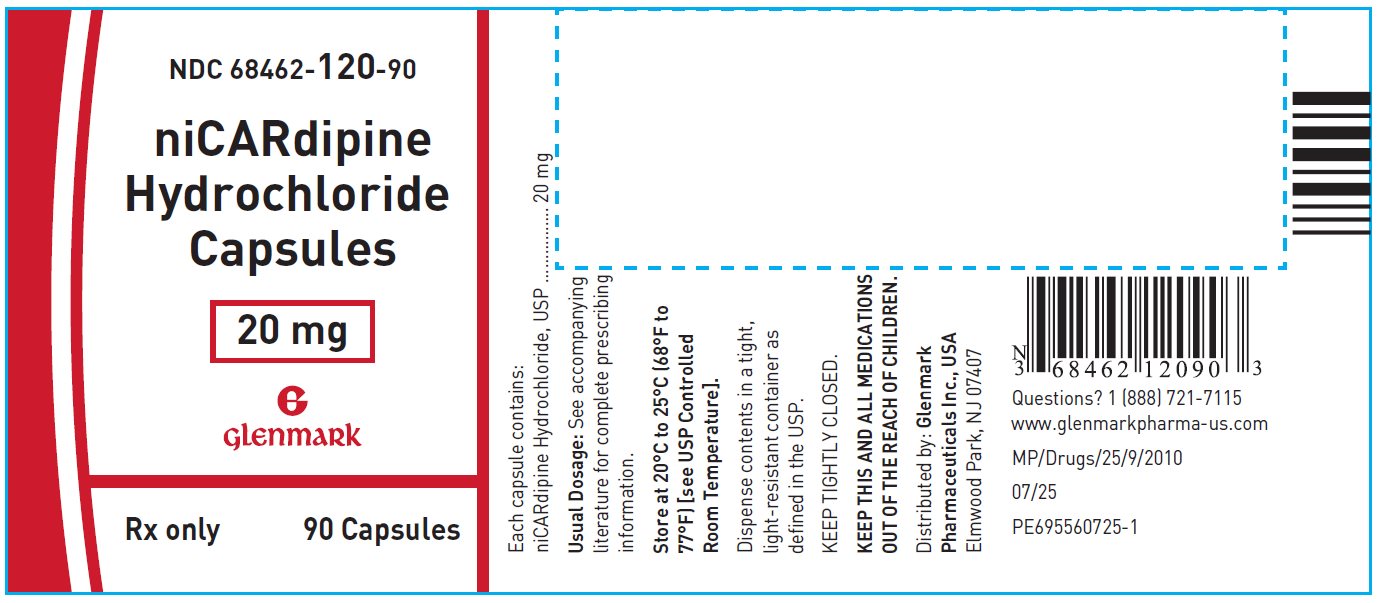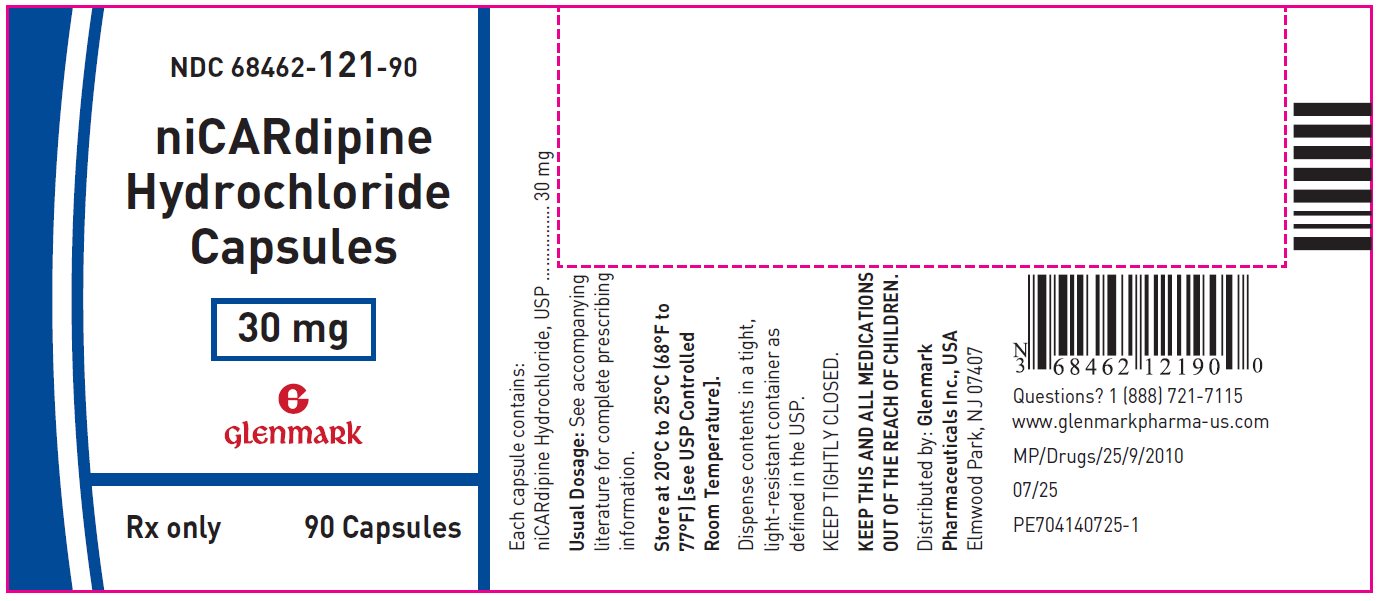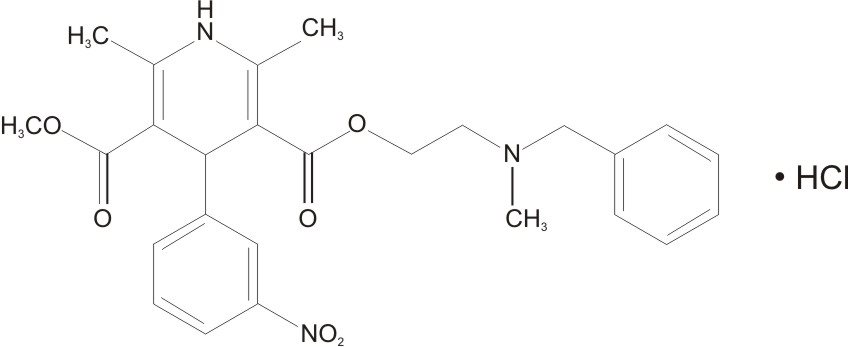 DRUG LABEL: Nicardipine Hydrochloride
NDC: 68462-120 | Form: CAPSULE
Manufacturer: Glenmark Pharmaceuticals Inc., USA
Category: prescription | Type: HUMAN PRESCRIPTION DRUG LABEL
Date: 20260129

ACTIVE INGREDIENTS: NICARDIPINE HYDROCHLORIDE 20 mg/1 1
INACTIVE INGREDIENTS: MAGNESIUM STEARATE; STARCH, CORN; TITANIUM DIOXIDE; GELATIN, UNSPECIFIED; FD&C BLUE NO. 1; FERROSOFERRIC OXIDE; POTASSIUM HYDROXIDE; SHELLAC

Nicardipine Hydrochloride Capsules

Rx only

DESCRIPTION

Nicardipine Hydrochloride Capsules for oral administration each contain 20 mg or 30 mg of nicardipine hydrochloride, USP. Nicardipine Hydrochloride Capsules are a calcium ion influx inhibitor (slow channel blocker or calcium channel blocker).

Nicardipine hydrochloride, USP is a dihydropyridine structure with the IUPAC (International Union of Pure and Applied Chemistry) chemical name 2-(benzyl-methyl amino)ethyl methyl 1,4-dihydro-2,6-dimethyl-4-(m‑nitrophenyl)-3,5-pyridinedicarboxylate monohydrochloride, and it has the following structure:

Nicardipine Hydrochloride, USP

Molecular Formula C26H29N3O6. HCl

Nicardipine hydrochloride, USP is a pale greenish-yellow, odorless, crystalline powder that melts at about 167°C to 171°C. It is freely soluble in methanol and acetic acid, sparingly soluble in ethanol, slightly soluble in water. It has a molecular weight of 515.99.

Each Nicardipine Hydrochloride Capsules, for oral administration, contains 20 mg or 30 mg nicardipine hydrochloride, USP. In addition, each capsule contains the following inactive ingredients: magnesium stearate, pregelatinized starch, titanium dioxide, gelatin and FD&C blue #1. The black printing ink contains black iron oxide, potassium hydroxide and shellac.

CLINICAL PHARMACOLOGY

Mechanism of Action

Nicardipine hydrochloride is a calcium entry blocker (slow channel blocker or calcium ion antagonist) that inhibits the transmembrane influx of calcium ions into cardiac muscle and smooth muscle without changing serum calcium concentrations. The contractile processes of cardiac muscle and vascular smooth muscle are dependent upon the movement of extracellular calcium ions into these cells through specific ion channels. The effects of nicardipine hydrochloride are more selective to vascular smooth muscle than cardiac muscle. In animal models, nicardipine hydrochloride produces relaxation of coronary vascular smooth muscle at drug levels that cause little or no negative inotropic effect.

Pharmacokinetics and Metabolism

Nicardipine hydrochloride is completely absorbed following oral doses administered as capsules. Plasma levels are detectable as early as 20 minutes following an oral dose and maximal plasma levels are observed within 30 minutes to 2 hours (mean Tmax = 1 hour). While nicardipine hydrochloride is completely absorbed, it is subject to saturable first pass metabolism and the systemic bioavailability is about 35% following a 30-mg oral dose at steady-state.

When nicardipine hydrochloride was administered 1 or 3 hours after a high-fat meal, the mean Cmax and mean AUC were lower (20% to 30%) than when nicardipine hydrochloride was given to fasting subjects. These decreases in plasma levels observed following a meal may be significant, but the clinical trials establishing the efficacy and safety of nicardipine hydrochloride were done in patients without regard to the timing of meals. Thus, the results of these trials reflect the effects of meal-induced variability.

The pharmacokinetics of nicardipine hydrochloride are nonlinear due to saturable hepatic first pass metabolism. Following oral administration, increasing doses result in a disproportionate increase in plasma levels. Steady-state Cmax values following 20-, 30-, and 40-mg doses every 8 hours averaged 36, 88, and 133 ng/mL, respectively. Hence, increasing the dose from 20 to 30 mg every 8 hours more than doubled Cmax and increasing the dose from 20 to 40 mg every 8 hours increased Cmax more than threefold. A similar disproportionate increase in AUC with dose was observed. Considerable inter-subject variability in plasma levels was also observed.

Post-absorption kinetics of nicardipine hydrochloride are also non-linear, although there is a reproducible terminal plasma half-life that averaged 8.6 hours following 30- and 40-mg doses at steady-state (tid). The terminal half-life represents the elimination of less than 5% of the absorbed drug (measured by plasma concentrations).

Elimination over the first 8 hours after dosing is much faster with a half-life of 2 to 4 hours. Steady-state plasma levels are achieved after 2 to 3 days of tid dosing (every 8 hours) and are twofold higher than after a single dose.

Nicardipine hydrochloride is highly protein bound (>95%) in human plasma over a wide concentration range.

Nicardipine hydrochloride is metabolized extensively by the hepatic cytochrome P450 enzymes, CYP2C8, 2D6, and 3A4; less than 1% of intact drug is detected in the urine. Following a radioactive oral dose in solution, 60% of the radioactivity was recovered in the urine and 35% in feces. Most of the dose (over 90%) was recovered within 48 hours of dosing. Nicardipine hydrochloride does not induce its own metabolism, however, nicardipine causes inhibition of certain cytochrome P450 enzymes (including CYP3A4, CYP2D6, CYP2C8, and CYP2C19). Inhibition of these enzymes may result in increased plasma levels of certain drugs, including cyclosporine and tacrolimus (see Drug Interactions). The altered pharmacokinetics may necessitate dosage adjustment of the affected drug or discontinuation of treatment.

Nicardipine hydrochloride plasma levels were higher in patients with mild renal impairment (baseline serum creatinine concentration ranged from 1.2 to 5.5 mg/dL) than in normal subjects. After 30-mg nicardipine hydrochloride tid at steady- state, Cmax and AUC were approximately twofold higher in these patients.

Because nicardipine hydrochloride is extensively metabolized by the liver, the plasma levels of the drug are influenced by changes in hepatic function. Nicardipine hydrochloride plasma levels were higher in patients with severe liver disease (hepatic cirrhosis confirmed by liver biopsy or presence of endoscopically-confirmed esophageal varices) than in normal subjects. After 20-mg nicardipine hydrochloride bid at steady-state, Cmax and AUC were 1.8 and fourfold higher, and the terminal half-life was prolonged to 19 hours in these patients.

Geriatric Pharmacokinetics

The steady-state pharmacokinetics of nicardipine hydrochloride in elderly hypertensive patients (≥65 years) are similar to those obtained in young normal adults. After 1 week of nicardipine hydrochloride dosing at 20 mg three times a day, the Cmax, Tmax, AUC, terminal plasma half-life and the extent of protein binding of nicardipine hydrochloride observed in healthy elderly hypertensive patients did not differ significantly from those observed in young normal volunteers.

Hemodynamics

In man, nicardipine hydrochloride produces a significant decrease in systemic vascular resistance. The degree of vasodilation and the resultant hypotensive effects are more prominent in hypertensive patients. In hypertensive patients, nicardipine reduces the blood pressure at rest and during isometric and dynamic exercise. In normotensive patients, a small decrease of about 9 mm Hg in systolic and 7 mm Hg in diastolic blood pressure may accompany this fall in peripheral resistance. An increase in heart rate may occur in response to the vasodilation and decrease in blood pressure, and in a few patients this heart rate increase may be pronounced. In clinical studies mean heart rate at time of peak plasma levels was usually increased by 5 to 10 beats per minute compared to placebo, with the greater increases at higher doses, while there was no difference from placebo at the end of the dosing interval. Hemodynamic studies following intravenous dosing in patients with coronary artery disease and normal or moderately abnormal left ventricular function have shown significant increases in ejection fraction and cardiac output with no significant change, or a small decrease, in left ventricular end- diastolic pressure (LVEDP). Although there is evidence that nicardipine hydrochloride increases coronary blood flow, there is no evidence that this property plays any role in its effectiveness in stable angina. In patients with coronary artery disease, intracoronary administration of nicardipine caused no direct myocardial depression. Nicardipine hydrochloride does, however, have a negative inotropic effect in some patients with severe left ventricular dysfunction and could, in patients with very impaired function, lead to worsened failure.

"Coronary Steal," the detrimental redistribution of coronary blood flow in patients with coronary artery disease (diversion of blood from underperfused areas toward better perfused areas), has not been observed during nicardipine treatment. On the contrary, nicardipine has been shown to improve systolic shortening in normal and hypokinetic segments of myocardial muscle, and radio-nuclide angiography has confirmed that wall motion remained improved during an increase in oxygen demand. Nonetheless, occasional patients have developed increased angina upon receiving nicardipine. Whether this represents steal in those patients, or is the result of increased heart rate and decreased diastolic pressure, is not clear.

In patients with coronary artery disease nicardipine improves L.V. diastolic distensibility during the early filling phase, probably due to a faster rate of myocardial relaxation in previously underperfused areas. There is little or no effect on normal myocardium, suggesting the improvement is mainly by indirect mechanisms such as afterload reduction, and reduced ischemia. Nicardipine has no negative effect on myocardial relaxation at therapeutic doses. The clinical consequences of these properties are as yet undemonstrated.

Electrophysiologic Effects

In general, no detrimental effects on the cardiac conduction system were seen with the use of nicardipine hydrochloride.

Nicardipine hydrochloride increased the heart rate when given intravenously during acute electrophysiologic studies and prolonged the corrected QT interval to a minor degree. The sinus node recovery times and SA conduction times were not affected by the drug. The PA, AH, and HV intervals^1 and the functional and effective refractory periods of the atrium were not prolonged by nicardipine hydrochloride, and the relative and effective refractory periods of the His-Purkinje system were slightly shortened after intravenous nicardipine hydrochloride.

^1 PA = conduction time from high to low right atrium, AH = conduction time from low right atrium to His bundle deflection or AV nodal conduction time, HV = conduction time through the His bundle and the bundle branch-Purkinje system.

Renal Function

There is a transient increase in electrolyte excretion, including sodium. nicardipine hydrochloride does not cause generalized fluid retention, as measured by weight changes, although 7% to 8% of the patients experience pedal edema.

Effects in Angina Pectoris

In controlled clinical trials of up to 12 weeks' duration in patients with chronic stable angina, nicardipine hydrochloride increased exercise tolerance and reduced nitroglycerin consumption and the frequency of anginal attacks. The antianginal efficacy of nicardipine hydrochloride (20 to 40 mg) has been demonstrated in four placebo-controlled studies involving 258 patients with chronic stable angina. In exercise tolerance testing, nicardipine hydrochloride significantly increased time to angina, total exercise duration and time to 1 mm ST segment depression. Included among these four studies was a dose-definition study in which dose-related improvements in exercise tolerance at 1 and 4 hours postdosing and reduced frequency of anginal attacks were seen at doses of 10, 20, and 30 mg tid. Effectiveness at 10 mg tid was, however, marginal. In a fifth placebo-controlled study, the antianginal efficacy of nicardipine hydrochloride was demonstrated at 8 hours postdose (trough). The sustained efficacy of nicardipine hydrochloride has been demonstrated over long-term dosing. Blood pressure fell in patients with angina by about 10/8 mm Hg at peak blood levels and was little different from placebo at trough blood levels.

Effects in Hypertension

Nicardipine hydrochloride produced dose-related decreases in both systolic and diastolic blood pressure in clinical trials. The antihypertensive efficacy of nicardipine hydrochloride administered three times daily has been demonstrated in three placebo-controlled studies involving 517 patients with mild to moderate hypertension.

The blood pressure responses in the three studies were statistically significant from placebo at peak (1 hour postdosing) and trough (8 hours postdosing) although it is apparent that well over half of the antihypertensive effect is lost by the end of the dosing interval. The results from placebo controlled studies of nicardipine hydrochloride given three times daily are shown in the following table:

Table 1

SYSTOLIC BP (mm Hg) |  |  |  |  | DIASTOLIC BP (mm Hg)
Dose | Number of Patients | Mean Peak Response | Mean Trough Response | Trough/ Peak | Dose | Number of Patients | Mean Peak Response | Mean Trough Response | Trough/ Peak
20 mg | 50 | -10.3 | -4.9 | 48% | 20 mg | 50 | -10.6 | -4.6 | 43%
20 mg | 52 | -17.6 | -7.9 | 45% | 20 mg | 52 | -9 | -2.9 | 32%
30 mg | 45 | -14.5 | -7.2 | 50% | 30 mg | 45 | -12.8 | -4.9 | 38%
30 mg | 44 | -14.6 | -7.5 | 51% | 30 mg | 44 | -14.2 | -4.3 | 30%
40 mg | 50 | -16.3 | -9.5 | 58% | 40 mg | 50 | -15.4 | -5.9 | 38%
40 mg | 38 | -15.9 | -6 | 38% | 40 mg | 38 | -14.8 | -3.7 | 25%

The responses are shown as differences from the concurrent placebo control group. The large changes between peak and trough effects were not accompanied by observed side effects at peak response times. In a study using 24-hour intra-arterial blood pressure monitoring, the circadian variation in blood pressure remained unaltered, but the systolic and diastolic blood pressures were reduced throughout the whole 24 hours.

When added to beta-blocker therapy, nicardipine hydrochloride further lowers both systolic and diastolic blood pressure.

INDICATIONS AND USAGE

I. Stable Angina

Nicardipine hydrochloride capsules are indicated for the management of patients with chronic stable angina (effort-associated angina). Nicardipine hydrochloride capsules may be used alone or in combination with beta-blockers.

II. Hypertension

Nicardipine hydrochloride capsules are indicated for the treatment of hypertension. Nicardipine hydrochloride capsules may be used alone or in combination with other antihypertensive drugs. In administering nicardipine it is important to be aware of the relatively large peak to trough differences in blood pressure effect (see DOSAGE AND ADMINISTRATION).

CONTRAINDICATIONS

Nicardipine hydrochloride capsules are contraindicated in patients with hypersensitivity to the drug.

Because part of the effect of nicardipine hydrochloride capsules are secondary to reduced afterload, the drug is also contraindicated in patients with advanced aortic stenosis. Reduction of diastolic pressure in these patients may worsen rather than improve myocardial oxygen balance.

WARNINGS

Increased Angina

About 7% of patients in short-term, placebo-controlled angina trials have developed increased frequency, duration or severity of angina on starting nicardipine hydrochloride or at the time of dosage increases, compared with 4% of patients on placebo. Comparisons with beta-blockers also show a greater frequency of increased angina, 4% vs 1%. The mechanism of this effect has not been established (see ADVERSE REACTIONS).

Use in Patients with Congestive Heart Failure

Although preliminary hemodynamic studies in patients with congestive heart failure have shown that nicardipine hydrochloride reduced afterload without impairing myocardial contractility, it has a negative inotropic effect in vitro and in some patients. Caution should be exercised when using the drug in congestive heart failure patients, particularly in combination with a beta-blocker.

Beta-Blocker Withdrawal

Nicardipine hydrochloride is not a beta-blocker and therefore gives no protection against the dangers of abrupt beta-blocker withdrawal; any such withdrawal should be by gradual reduction of the dose of beta-blocker, preferably over 8 to 10 days.

PRECAUTIONS

General

Blood Pressure

Because nicardipine hydrochloride decreases peripheral resistance, careful monitoring of blood pressure during the initial administration and titration of nicardipine hydrochloride is suggested.

Nicardipine hydrochloride, like other calcium channel blockers, may occasionally produce symptomatic hypotension. Caution is advised to avoid systemic hypotension when administering the drug to patients who have sustained an acute cerebral infarction or hemorrhage. Because of prominent effects at the time of peak blood levels, initial titration should be performed with measurements of blood pressure at peak effect (1 to 2 hours after dosing) and just before the next dose.

Use in Patients with Impaired Hepatic Function

Since the liver is the major site of biotransformation and since nicardipine hydrochloride is subject to first pass metabolism, the drug should be used with caution in patients having impaired liver function or reduced hepatic blood flow. Patients with severe liver disease developed elevated blood levels (fourfold increase in AUC) and prolonged half-life (19 hours) of nicardipine hydrochloride (see DOSAGE AND ADMINISTRATION).

Use in Patients with Impaired Renal Function

When nicardipine hydrochloride 20 mg or 30 mg tid was given to hypertensive patients with mild renal impairment, mean plasma concentrations, AUC and Cmax were approximately twofold higher in renally impaired patients than in healthy controls. Doses in these patients must be adjusted (see CLINICAL PHARMACOLOGY and DOSAGE AND ADMINISTRATION).

DRUG INTERACTIONS

Drug Interactions

Beta-Blockers

In controlled clinical studies, adrenergic beta-receptor blockers have been frequently administered concomitantly with nicardipine hydrochloride. The combination is well tolerated.

Cimetidine

Cimetidine increases nicardipine hydrochloride plasma levels. Patients receiving the two drugs concomitantly should be carefully monitored.

Digoxin

Some calcium blockers may increase the concentration of digitalis preparations in the blood. nicardipine hydrochloride usually does not alter the plasma levels of digoxin; however, serum digoxin levels should be evaluated after concomitant therapy with nicardipine hydrochloride is initiated.

Maalox®

Coadministration of Maalox TC had no effect on nicardipine hydrochloride absorption.

Fentanyl Anesthesia

Severe hypotension has been reported during fentanyl anesthesia with concomitant use of a beta-blocker and a calcium channel blocker. Even though such interactions were not seen during clinical studies with nicardipine hydrochloride, an increased volume of circulating fluids might be required if such an interaction were to occur.

Cyclosporine

Concomitant administration of oral or intravenous nicardipine and cyclosporine results in elevated plasma cyclosporine levels through nicardipine inhibition of hepatic microsomal enzymes, including CYP3A4. Plasma concentrations of cyclosporine should therefore be closely monitored, and its dosage reduced accordingly, in patients treated with nicardipine.

Tacrolimus

Concomitant administration of oral or intravenous nicardipine and tacrolimus may result in elevated plasma tacrolimus levels through nicardipine inhibition of hepatic microsomal enzymes, including CYP3A4. Closely monitor plasma concentrations of tacrolimus during nicardipine administration, and adjust the dose of tacrolimus accordingly.

When therapeutic concentrations of furosemide, propranolol, dipyridamole, warfarin, quinidine or naproxen were added to human plasma (in vitro), the plasma protein binding of nicardipine hydrochloride was not altered.

Carcinogenesis, Mutagenesis, Impairment of Fertility

Rats treated with nicardipine in the diet (at concentrations calculated to provide daily dosage levels of 5, 15 or 45 mg/kg/day) for 2 years showed a dose-dependent increase in thyroid hyperplasia and neoplasia (follicular adenoma/carcinoma). One- and 3-month studies in the rat have suggested that these results are linked to a nicardipine-induced reduction in plasma thyroxine (T4) levels with a consequent increase in plasma levels of thyroid stimulating hormone (TSH).

Chronic elevation of TSH is known to cause hyperstimulation of the thyroid. In rats on an iodine deficient diet, nicardipine administration for 1 month was associated with thyroid hyperplasia that was prevented by T4 supplementation. Mice treated with nicardipine in the diet (at concentrations calculated to provide daily dosage levels of up to 100 mg/kg/day) for up to 18 months showed no evidence of neoplasia of any tissue and no evidence of thyroid changes. There was no evidence of thyroid pathology in dogs treated with up to 25 mg nicardipine/kg/day for 1 year and no evidence of effects of nicardipine on thyroid function (plasma T4 and TSH) in man.

There was no evidence of a mutagenic potential of nicardipine in a battery of genotoxicity tests conducted on microbial indicator organisms, in micronucleus tests in mice and hamsters, or in a sister chromatid exchange study in hamsters.

No impairment of fertility was seen in male or female rats administered nicardipine at oral doses as high as 100 mg/kg/day (50 times the 40 mg tid maximum recommended antianginal or antihypertensive dose in man, assuming a patient weight of 60 kg).

Pregnancy

Nicardipine was embryocidal when administered orally to pregnant Japanese White rabbits, during organogenesis, at 150 mg/kg/day (a dose associated with marked body weight gain suppression in the treated doe) but not at 50 mg/kg/day (25 times the maximum recommended antianginal or antihypertensive dose in man). No adverse effects on the fetus were observed when New Zealand albino rabbits were treated, during organogenesis, with up to 100 mg nicardipine/kg/day (a dose associated with significant mortality in the treated doe). In pregnant rats administered nicardipine orally at up to 100 mg/kg/day (50 times the maximum recommended human dose) there was no evidence of embryolethality or teratogenicity. However, dystocia, reduced birth weights, reduced neonatal survival, and reduced neonatal weight gain were noted. There are no adequate and well-controlled studies in pregnant women. nicardipine hydrochloride should be used during pregnancy only if the potential benefit justifies the potential risk to the fetus.

Nursing Mothers

Studies in rats have shown significant concentrations of nicardipine hydrochloride in maternal milk following oral administration. For this reason it is recommended that women who wish to breastfeed should not take this drug.

Pediatric Use

Safety and efficacy in patients under the age of 18 have not been established.

Geriatric Use

Pharmacokinetic parameters did not differ between elderly hypertensive patients (≥65 years) and healthy controls after 1 week of nicardipine hydrochloride treatment at 20 mg tid. Plasma nicardipine hydrochloride concentrations in elderly hypertensive subjects were similar to plasma concentrations in healthy young adult subjects when nicardipine hydrochloride was administered at doses of 10, 20, and 30 mg tid, suggesting that the pharmacokinetics of nicardipine hydrochloride are similar in young and elderly hypertensive patients.

Clinical studies of nicardipine did not include sufficient numbers of subjects aged 65 and over to determine whether they respond differently from younger subjects. Other reported clinical experience has not identified differences in responses between the elderly and younger patients. In general, dose selection for an elderly patient should be cautious, usually starting at the low end of the dosing range, reflecting the greater frequency of decreased hepatic, renal, or cardiac function, and of concomitant disease or other drug therapy.

ADVERSE REACTIONS

In multiple-dose US and foreign controlled short-term (up to 3 months) studies 1910 patients received nicardipine hydrochloride alone or in combination with other drugs. In these studies adverse events were reported spontaneously; adverse experiences were generally not serious but occasionally required dosage adjustment and about 10% of patients left the studies prematurely because of them. Peak responses were not observed to be associated with adverse effects during clinical trials, but physicians should be aware that adverse effects associated with decreases in blood pressure (tachycardia, hypotension, etc.) could occur around the time of the peak effect. Most adverse effects were expected consequences of the vasodilator effects of nicardipine hydrochloride.

Angina

The incidence rates of adverse effects in anginal patients were derived from multicenter, controlled clinical trials. Following are the rates of adverse effects for nicardipine hydrochloride (n=520) and placebo (n=310), respectively, that occurred in 0.4% of patients or more. These represent events considered probably drug-related by the investigator (except for certain cardiovascular events that were recorded in a different category). Where the frequency of adverse effects for nicardipine hydrochloride and placebo is similar, causal relationship is uncertain. The only dose-related effects were pedal edema and increased angina.

Table 2: Percent of Patients with Adverse Effects in Controlled Studies (Incidence of Discontinuations Shown in Parentheses)

Adverse Experience | Nicardipine Hydrochloride (n= 520) |  | PLACEBO (n= 310)
Pedal Edema | 7.1 | (0) | 0.3 | (0)
Dizziness | 6.9 | (1.2) | 0.6 | (0)
Headache | 6.4 | (0.6) | 2.6 | (0)
Asthenia | 5.8 | (0.4) | 2.6 | (0)
Flushing | 5.6 | (0.4) | 1 | (0)
Increased Angina | 5.6 | (3.5) | 4.2 | (1.9)
Palpitations | 3.3 | (0.4) | 0 | (0)
Nausea | 1.9 | (0) | 0.3 | (0)
Dyspepsia | 1.5 | (0.6) | 0.6 | (0.3)
Dry Mouth | 1.4 | (0) | 0.3 | (0)
Somnolence | 1.4 | (0) | 1 | (0)
Rash | 1.2 | (0.2) | 0.3 | (0)
Tachycardia | 1.2 | (0.2) | 0.6 | (0)
Myalgia | 1 | (0) | 0 | (0)
Other Edema | 1 | (0) | 0 | (0)
Paresthesia | 1 | (0.2) | 0.3 | (0)
Sustained Tachycardia | 0.8 | (0.6) | 0 | (0)
Syncope | 0.8 | (0.2) | 0 | (0)
Constipation | 0.6 | (0.2) | 0.6 | (0)
Dyspnea | 0.6 | (0) | 0 | (0)
Abnormal ECG | 0.6 | (0.6) | 0 | (0)
Malaise | 0.6 | (0) | 0 | (0)
Nervousness | 0.6 | (0) | 0.3 | (0)
Tremor | 0.6 | (0) | 0 | (0)

In addition, adverse events were observed that are not readily distinguishable from the natural history of the atherosclerotic vascular disease in these patients. Adverse events in this category each occurred in <0.4% of patients receiving nicardipine hydrochloride and included myocardial infarction, atrial fibrillation, exertional hypotension, pericarditis, heart block, cerebral ischemia, and ventricular tachycardia. It is possible that some of these events were drug-related.

Hypertension

The incidence rates of adverse effects in hypertensive patients were derived from multicenter, controlled clinical trials. Following are the rates of adverse effects for nicardipine hydrochloride (n=1,390) and placebo (n=211), respectively, that occurred in 0.4% of patients or more. These represent events considered probably drug-related by the investigator. Where the frequency of adverse effects for nicardipine hydrochloride and placebo is similar, causal relationship is uncertain. The only dose-related effect was pedal edema.

Table 3: Percent of Patients with Adverse Effects in Controlled Studies (Incidence of discontinuations shown in parentheses)

Adverse Experience | Nicardipine Hydrochloride (n = 1,390) |  | PLACEBO (n = 211)
Flushing | 9.7 | (2.1) | 2.8 | (0)
Headache | 8.2 | (2.6) | 4.7 | (0)
Pedal Edema | 8 | (1.8) | 0.9 | (0)
Asthenia | 4.2 | (1.7) | 0.5 | (0)
Palpitations | 4.1 | (1) | 0 | (0)
Dizziness | 4 | (1.8) | 0 | (0)
Tachycardia | 3.4 | (1.2) | 0.5 | (0)
Nausea | 2.2 | (0.9) | 0.9 | (0)
Somnolence | 1.1 | (0.1) | 0 | (0)
Dyspepsia | 0.8 | (0.3) | 0.5 | (0)
Insomnia | 0.6 | (0.1) | 0 | (0)
Malaise | 0.6 | (0.1) | 0 | (0)
Other Edema | 0.6 | (0.3) | 1.4 | (0)
Abnormal Dreams | 0.4 | (0) | 0 | (0)
Dry Mouth | 0.4 | (0.1) | 0 | (0)
Nocturia | 0.4 | (0) | 0 | (0)
Rash | 0.4 | (0.4) | 0 | (0)
Vomiting | 0.4 | (0.4) | 0 | (0)

Rare Events

The following rare adverse events have been reported in clinical trials or the literature:

Body as a Whole: infection, allergic reaction

Cardiovascular: hypotension, postural hypotension, atypical chest pain, peripheral vascular disorder, ventricular extrasystoles, ventricular tachycardia

Digestive: sore throat, abnormal liver chemistries

Musculoskeletal: arthralgia

Nervous: hot flashes, vertigo, hyperkinesia, impotence, depression, confusion, anxiety

Respiratory: rhinitis, sinusitis

Special Senses: tinnitus, abnormal vision, blurred vision

Urogenital: increased urinary frequency

OVERDOSAGE

Overdosage with a 600-mg single dose (15 to 30 times normal clinical dose) has been reported. Marked hypotension (blood pressure unobtainable) and bradycardia (heart rate 20 bpm in normal sinus rhythm) occurred, along with drowsiness, confusion and slurred speech. Supportive treatment with a vasopressor resulted in gradual improvement with normal vital signs approximately 9 hours posttreatment.

Based on results obtained in laboratory animals, overdosage may cause systemic hypotension, bradycardia (following initial tachycardia) and progressive atrioventricular conduction block. Reversible hepatic function abnormalities and sporadic focal hepatic necrosis were noted in some animal species receiving very large doses of nicardipine.

For treatment of overdose standard measures (for example, evacuation of gastric contents, elevation of extremities, attention to circulating fluid volume, and urine output) including monitoring of cardiac and respiratory functions should be implemented. The patient should be positioned so as to avoid cerebral anoxia. Frequent blood pressure determinations are essential. Vasopressors are clinically indicated for patients exhibiting profound hypotension. Intravenous calcium gluconate may help reverse the effects of calcium entry blockade.

DOSAGE AND ADMINISTRATION

Angina

The dose should be individually titrated for each patient beginning with 20 mg three times daily. Doses in the range of 20 to 40 mg three times a day have been shown to be effective. At least 3 days should be allowed before increasing the nicardipine hydrochloride capsules dose to ensure achievement of steady-state plasma drug concentrations.

Concomitant Use with Other Antianginal Agents

1. Sublingual NTG may be taken as required to abort acute anginal attacks during nicardipine hydrochloride capsules therapy.

2. Prophylactic Nitrate Therapy: Nicardipine hydrochloride capsules may be safely coadministered with short- and long-acting nitrates.

3. Beta-blockers: Nicardipine hydrochloride capsules may be safely coadministered with beta-blockers (see Drug Interactions).

Hypertension

The dose of nicardipine hydrochloride should be individually adjusted according to the blood pressure response beginning with 20 mg three times daily. The effective doses in clinical trials have ranged from 20 mg to 40 mg three times daily. The maximum blood pressure lowering effect occurs approximately 1 to 2 hours after dosing. To assess the adequacy of blood pressure response, the blood pressure should be measured at trough (8 hours after dosing). Because of the prominent peak effects of nicardipine, blood pressure should be measured 1 to 2 hours after dosing, particularly during initiation of therapy (see PRECAUTIONS: Blood Pressure, INDICATIONS and CLINICAL PHARMACOLOGY: Effects in Hypertension). At least 3 days should be allowed before increasing the nicardipine hydrochloride dose to ensure achievement of steady-state plasma drug concentrations.

Concomitant Use with Other Antihypertensive Agents

1. Diuretics: Nicardipine hydrochloride capsules may be safely coadministered with thiazide diuretics.

2. Beta-blockers: Nicardipine hydrochloride capsules may be safely coadministered with beta-blockers (see Drug Interactions).

Special Patient Populations

Renal Insufficiency

Although there is no evidence that nicardipine hydrochloride impairs renal function, careful dose titration beginning with 20 mg tid is advised (see PRECAUTIONS).

Hepatic Insufficiency

Nicardipine hydrochloride should be administered cautiously in patients with severely impaired hepatic function. A suggested starting dose of 20 mg twice a day is advised with individual titration based on clinical findings maintaining the twice a day schedule (see PRECAUTIONS).

Congestive Heart Failure

Caution is advised when titrating nicardipine hydrochloride dosage in patients with congestive heart failure (see WARNINGS).

HOW SUPPLIED

Nicardipine Hydrochloride Capsules 20 mg are available in size ‘3’ hard gelatin capsules with a light blue opaque cap and a white opaque body, imprinted with “Y” on the cap and “120” on the body in black ink and filled with yellow powder. These are supplied as follows:

Bottles of 90 Capsules, NDC 68462-120-90

Bottles of 500 Capsules, NDC 68462-120-05

Nicardipine Hydrochloride Capsules 30 mg are available in size ‘2’ hard gelatin capsules with a blue opaque cap and a light blue opaque body, imprinted with “Y” on the cap and “121” on the body in black ink and filled with yellow powder. These are supplied as follows:

Bottles of 90 Capsules, NDC 68462-121-90

Bottles of 500 Capsules, NDC 68462-121-05

Store at 20°C to 25°C (68°F to 77°F) [see USP Controlled Room Temperature]. Dispense contents in a tight, light-resistant container as defined in the USP.

All trademarks are the property of their respective owners.

Distributed by:

Glenmark Pharmaceuticals Inc., USA

Elmwood Park, NJ 07407

Questions? 1 (888) 721-7115

www.glenmarkpharma-us.com

August 2025

PACKAGE/LABEL PRINCIPAL DISPLAY PANEL- 20 mg, 90’s Count

NDC 68462-120-90

niCARdipine Hydrochloride Capsules

20 mg

Rx Only

90 Capsules

Package/Label Display Panel- 30 mg, 90’s Count

NDC 68462-121-90

niCARdipine Hydrochloride Capsules

30 mg

Rx Only

90 Capsules